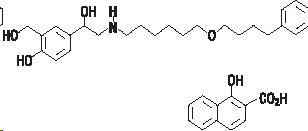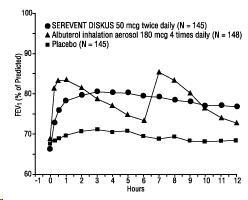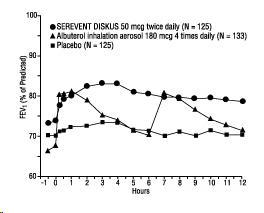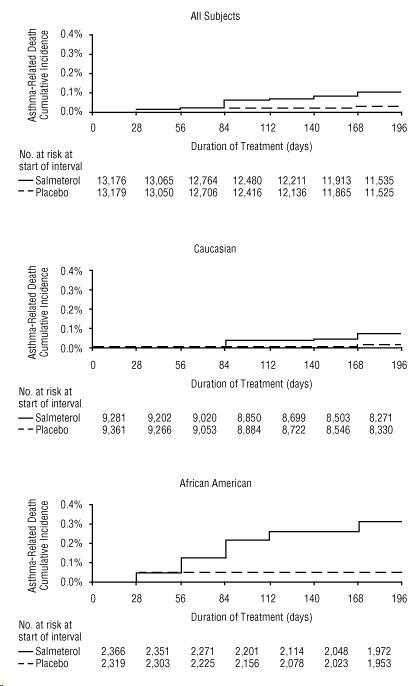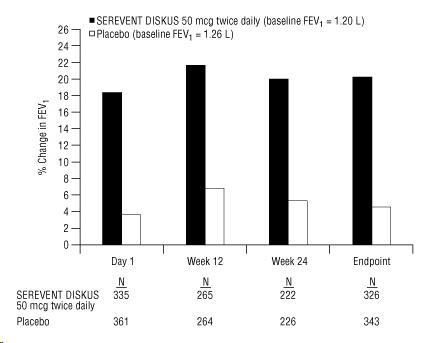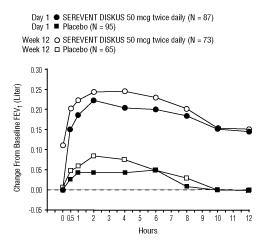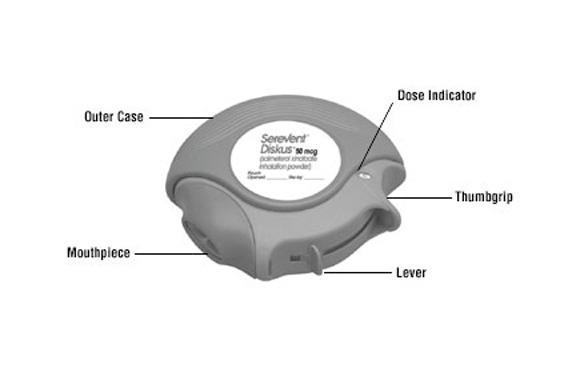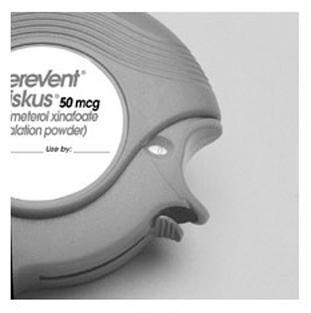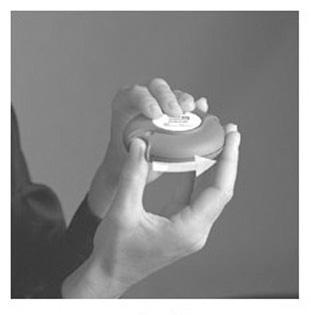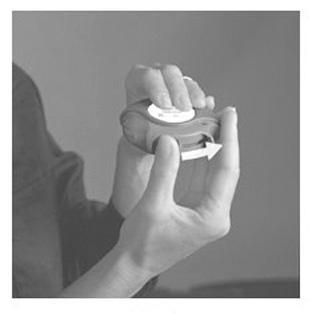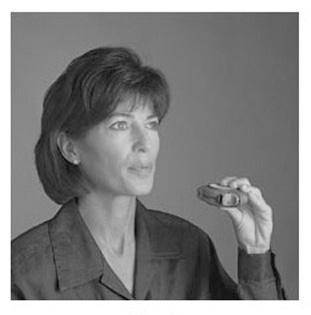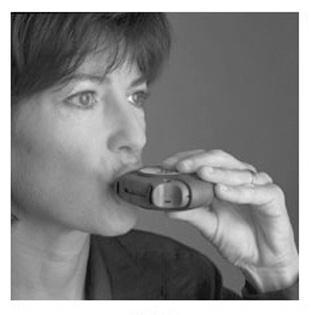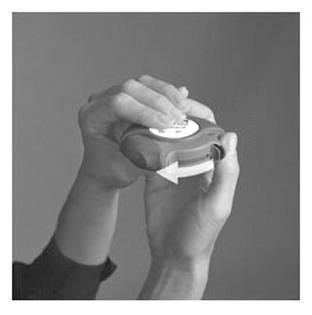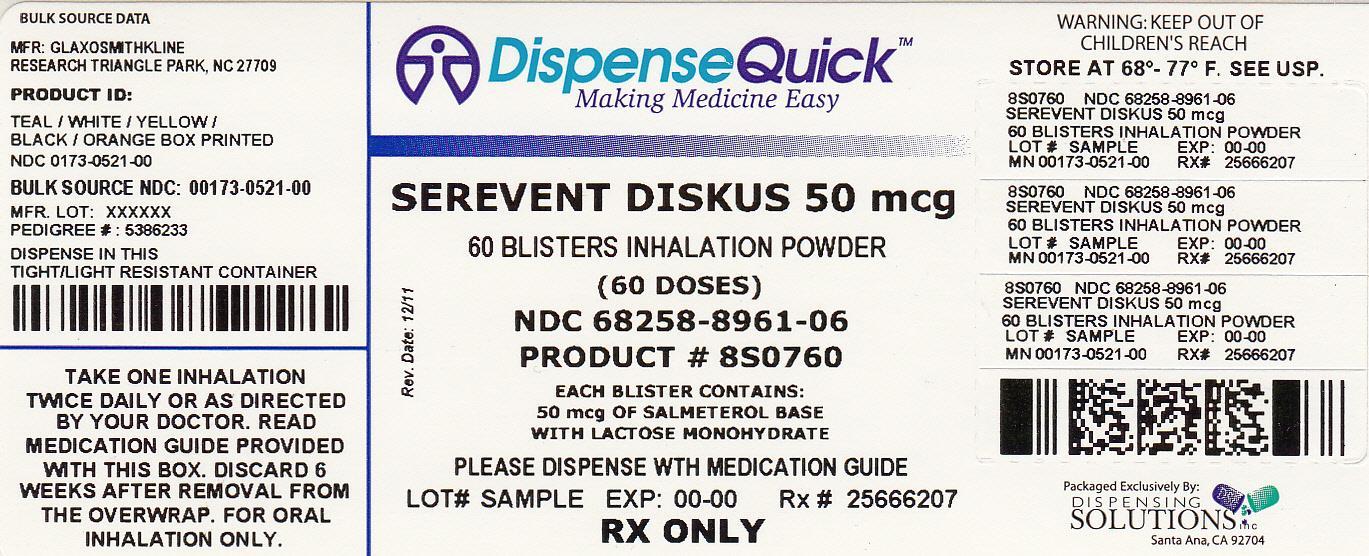 DRUG LABEL: SEREVENT
NDC: 68258-8961 | Form: POWDER, METERED
Manufacturer: Dispensing Solutions, Inc.
Category: prescription | Type: HUMAN PRESCRIPTION DRUG LABEL
Date: 20120927

ACTIVE INGREDIENTS: SALMETEROL XINAFOATE 50 ug/1 1
INACTIVE INGREDIENTS: LACTOSE

HIGHLIGHTS OF PRESCRIBING INFORMATION

These highlights do not include all the information needed to use SEREVENT DISKUS safely and effectively. See full prescribing information for SEREVENT DISKUS.
SEREVENT DISKUS
(salmeterol xinafoate inhalation powder)
FOR ORAL INHALATION
Initial U.S. Approval: 1994

RECENT MAJOR CHANGES

Boxed Warning | December 2010
Indications and Usage (1.1, 1.2) | December 2010
Dosage and Administration (2.1, 2.2) | December 2010
Warnings and Precautions, Asthma-Related Death (5.1) | December 2010

WARNING: ASTHMA-RELATED DEATH

See full prescribing information for complete boxed warning

- Long-acting beta2-adrenergic agonists (LABA), such as salmeterol, the active ingredient in SEREVENT DISKUS, increase the risk of asthma-related death. A US study showed an increase in asthma-related deaths in patients receiving salmeterol (13 deaths out of 13,176 patients treated for 28 weeks on salmeterol versus 3 out of 13,179 patients on placebo). Currently available data are inadequate to determine whether concurrent use of inhaled corticosteroids or other long-term asthma control drugs mitigates the increased risk of asthma-related death from LABA. (5.1)
- Prescribe SEREVENT DISKUS only as additional therapy for patients with asthma who are currently taking but are inadequately controlled on a long-term asthma control medication, such as an inhaled corticosteroid. Once asthma control is achieved and maintained, assess the patient at regular intervals and step down therapy (e.g., discontinue SEREVENT DISKUS) if possible without loss of asthma control and maintain the patient on a long-term asthma control medication, such as an inhaled corticosteroid. Do not use SEREVENT DISKUS for patients whose asthma is adequately controlled on low- or medium-dose inhaled corticosteroids. (1.1, 5.1)
- Available data from controlled clinical trials suggest that LABA increase the risk of asthma-related hospitalization in pediatric and adolescent patients. (5.1)

1 INDICATIONS AND USAGE

SEREVENT DISKUS is a LABA indicated for:

- Treatment of asthma in patients aged 4 years and older. (1.1)
- Prevention of exercise-induced bronchospasm (EIB) in patients aged 4 years and older. (1.2)
- Maintenance treatment of bronchospasm associated with chronic obstructive pulmonary disease (COPD). (1.3)

Important limitation:

- Not indicated for the relief of acute bronchospasm. (1.1, 1.3)

2 DOSAGE AND ADMINISTRATION

For oral inhalation only.

- Treatment of asthma in patients ≥4 years: 1 inhalation twice daily in addition to concomitant treatment with an inhaled corticosteroid. (2.1)
- EIB: One inhalation at least 30 minutes before exercise. (2.2)
- Maintenance treatment of bronchospasm associated with COPD: 1 inhalation twice daily. (2.3)

3 DOSAGE FORMS AND STRENGTHS

DISKUS device containing salmeterol (50 mcg) as an oral inhalation powder. (3)

4 CONTRAINDICATIONS

- Asthma: Without concomitant use of a long-term asthma control medication such as an inhaled corticosteroid. (4)
- Primary treatment of status asthmaticus or acute episodes of asthma or COPD requiring intensive measures. (4)
- Severe hypersensitivity to milk proteins. (4)

5 WARNINGS AND PRECAUTIONS

- Asthma-related death and asthma-related hospitalizations: Long-acting beta2-adrenergic agonists increase the risk. Prescribe for asthma only as concomitant therapy with an inhaled corticosteroid. (5.1)
- Deterioration of disease and acute episodes: Do not initiate during rapidly deteriorating asthma. Do not use to treat acute symptoms. (5.2)
- Corticosteroids: Not a substitute for corticosteroids. Patients with asthma must take a concomitant inhaled corticosteroid. (5.3)
- Use with additional long-acting beta2-agonist: Do not use in combination because of risk of overdose. (5.4)
- Paradoxical bronchospasm: Discontinue SEREVENT DISKUS and institute alternative therapy if paradoxical bronchospasm occurs. (5.5)
- Patients with cardiovascular or central nervous system disorders: Use with caution because of beta-adrenergic stimulation. (5.6)
- Strong cytochrome P450 3A4 inhibitors (e.g., ketoconazole): Risk of cardiovascular effects. Use not recommended with SEREVENT DISKUS. (5.8)
- Coexisting conditions: Use with caution in patients with convulsive disorders, thyrotoxicosis, diabetes mellitus, and ketoacidosis. (5.9)
- Metabolic effects: Be alert to hypokalemia and hyperglycemia. (5.10)

6 ADVERSE REACTIONS

The most common adverse reactions (incidence ≥5%) are:

- Asthma: Headache, influenza, nasal/sinus congestion, pharyngitis, rhinitis tracheitis/bronchitis. (6.1)
- COPD: Cough, headache, musculoskeletal pain, throat irritation, viral respiratory infection. (6.2)

To report SUSPECTED ADVERSE REACTIONS, contact GlaxoSmithKline at 1-888-825-5249 or FDA at 1-800-FDA-1088 or www.fda.gov/medwatch

7 DRUG INTERACTIONS

- Strong cytochrome P450 3A4 inhibitors (e.g., ritonavir): Use not recommended. May increase risk of cardiovascular effects. (7.1)
- Monoamine oxidase inhibitors and tricyclic antidepressants: Use with extreme caution. May potentiate effect of salmeterol on vascular system. (7.2)
- Beta-blockers: Use with caution. May block bronchodilatory effects of beta-agonists and produce severe bronchospasm. (7.3)
- Diuretics: Use with caution. Electrocardiographic changes and/or hypokalemia associated with nonpotassium-sparing diuretics may worsen with concomitant beta-agonists. (7.4)

8 USE IN SPECIFIC POPULATIONS

Hepatic impairment: Monitor patients for signs of increased drug exposure. (8.6)

FULL PRESCRIBING INFORMATION

WARNING: ASTHMA-RELATED DEATH

Long-acting beta2-adrenergic agonists (LABA), such as salmeterol, the active ingredient in SEREVENT® DISKUS®, increase the risk of asthma-related death. Data from a large placebo-controlled US study that compared the safety of salmeterol (SEREVENT® Inhalation Aerosol) or placebo added to usual asthma therapy showed an increase in asthma-related deaths in patients receiving salmeterol (13 deaths out of 13,176 patients treated for 28 weeks on salmeterol versus 3 deaths out of 13,179 patients on placebo). Currently available data are inadequate to determine whether concurrent use of inhaled corticosteroids or other long-term asthma control drugs mitigates the increased risk of asthma-related death from LABA.

Because of this risk, use of SEREVENT DISKUS for the treatment of asthma without a concomitant long-term asthma control medication, such as an inhaled corticosteroid, is contraindicated. Use SEREVENT DISKUS only as additional therapy for patients with asthma who are currently taking but are inadequately controlled on a long-term asthma control medication, such as an inhaled corticosteroid. Once asthma control is achieved and maintained, assess the patient at regular intervals and step down therapy (e.g., discontinue SEREVENT DISKUS) if possible without loss of asthma control and maintain the patient on a long-term asthma control medication, such as an inhaled corticosteroid. Do not use SEREVENT DISKUS for patients whose asthma is adequately controlled on low- or medium-dose inhaled corticosteroids.

Pediatric and Adolescent Patients: Available data from controlled clinical trials suggest that LABA increase the risk of asthma-related hospitalization in pediatric and adolescent patients. For pediatric and adolescent patients with asthma who require addition of a LABA to an inhaled corticosteroid, a fixed-dose combination product containing both an inhaled corticosteroid and a LABA should ordinarily be used to ensure adherence with both drugs. In cases where use of a separate long-term asthma control medication (e.g., inhaled corticosteroid) and a LABA is clinically indicated, appropriate steps must be taken to ensure adherence with both treatment components. If adherence cannot be assured, a fixed-dose combination product containing both an inhaled corticosteroid and a LABA is recommended.

1 INDICATIONS AND USAGE

1.1 Treatment of Asthma

SEREVENT DISKUS is indicated for the treatment of asthma and in the prevention of bronchospasm only as concomitant therapy with a long-term asthma control medication, such as an inhaled corticosteroid, in patients aged 4 years and older with reversible obstructive airway disease, including patients with symptoms of nocturnal asthma. LABA, such as salmeterol, the active ingredient in SEREVENT DISKUS, increase the risk of asthma-related death [see Warnings and Precautions (5.1)]. Use of SEREVENT DISKUS for the treatment of asthma without concomitant use of a long-term asthma control medication, such as an inhaled corticosteroid, is contraindicated [see Contraindications (4)]. Use SEREVENT DISKUS only as additional therapy for patients with asthma who are currently taking but are inadequately controlled on a long-term asthma control medication, such as an inhaled corticosteroid. Once asthma control is achieved and maintained, assess the patient at regular intervals and step down therapy (e.g., discontinue SEREVENT DISKUS) if possible without loss of asthma control and maintain the patient on a long-term asthma control medication, such as an inhaled corticosteroid. Do not use SEREVENT DISKUS for patients whose asthma is adequately controlled on low- or medium-dose inhaled corticosteroids.

Pediatric and Adolescent Patients: Available data from controlled clinical trials suggest that LABA increase the risk of asthma-related hospitalization in pediatric and adolescent patients. For pediatric and adolescent patients with asthma who require addition of a LABA to an inhaled corticosteroid, a fixed-dose combination product containing both an inhaled corticosteroid and a LABA should ordinarily be used to ensure adherence with both drugs. In cases where use of a separate long-term asthma control medication (e.g., inhaled corticosteroid) and a LABA is clinically indicated, appropriate steps must be taken to ensure adherence with both treatment components. If adherence cannot be assured, a fixed-dose combination product containing both an inhaled corticosteroid and a LABA is recommended.

Important Limitation of Use: SEREVENT DISKUS is NOT indicated for the relief of acute bronchospasm.

1.2 Prevention of Exercise-Induced Bronchospasm

SEREVENT DISKUS is also indicated for prevention of exercise-induced bronchospasm (EIB) in patients aged 4 years and older. Use of SEREVENT DISKUS as a single agent for the prevention of EIB may be clinically indicated in patients who do not have persistent asthma. In patients with persistent asthma, use of SEREVENT DISKUS for the prevention of EIB may be clinically indicated, but the treatment of asthma should include a long-term asthma control medication, such as an inhaled corticosteroid.

1.3 Maintenance Treatment of Chronic Obstructive Pulmonary Disease

SEREVENT DISKUS is indicated for the long-term twice-daily (morning and evening) administration in the maintenance treatment of bronchospasm associated with chronic obstructive pulmonary disease (COPD) (including emphysema and chronic bronchitis).

Important Limitation of Use: SEREVENT DISKUS is NOT indicated for the relief of acute bronchospasm.

2 DOSAGE AND ADMINISTRATION

SEREVENT DISKUS should be administered by the orally inhaled route only.

For both asthma and COPD, adverse effects are more likely to occur with higher doses of salmeterol, and more frequent administration or administration of a larger number of inhalations (more than 1 inhalation twice daily) is not recommended. Patients using SEREVENT DISKUS should not use additional LABA for any reason. [See Warnings and Precautions (5.4, 5.6).]

2.1 Asthma

LABA, such as salmeterol, the active ingredient in SEREVENT DISKUS, increase the risk of asthma-related death [see Warnings and Precautions (5.1)].

Because of this risk, use of SEREVENT DISKUS for the treatment of asthma without concomitant use of a long-term asthma control medication, such as an inhaled corticosteroid is contraindicated. Use SEREVENT DISKUS only as additional therapy for patients with asthma who are currently taking but are inadequately controlled on a long-term asthma control medication, such as an inhaled corticosteroid. Once asthma control is achieved and maintained, assess the patient at regular intervals and step down therapy (e.g., discontinue SEREVENT DISKUS) if possible without loss of asthma control and maintain the patient on a long-term asthma control medication, such as an inhaled corticosteroid. Do not use SEREVENT DISKUS for patients whose asthma is adequately controlled on low- or medium-dose inhaled corticosteroids.

Pediatric and Adolescent Patients: Available data from controlled clinical trials suggest that LABA increase the risk of asthma-related hospitalization in pediatric and adolescent patients. For patients with asthma less than 18 years of age who require addition of a LABA to an inhaled corticosteroid, a fixed-dose combination product containing both an inhaled corticosteroid and a LABA should ordinarily be used to ensure adherence with both drugs. In cases where use of a separate long-term asthma control medication (e.g., inhaled corticosteroid) and a LABA is clinically indicated, appropriate steps must be taken to ensure adherence with both treatment components. If adherence cannot be assured, a fixed-dose combination product containing both an inhaled corticosteroid and a LABA is recommended.

For bronchodilatation and prevention of symptoms of asthma, including the symptoms of nocturnal asthma, the usual dosage for adults and children aged 4 years and older is 1 inhalation (50 mcg) twice daily (morning and evening, approximately 12 hours apart). If a previously effective dosage regimen fails to provide the usual response, medical advice should be sought immediately as this is often a sign of destabilization of asthma. Under these circumstances, the therapeutic regimen should be reevaluated. If symptoms arise in the period between doses, an inhaled, short-acting beta2-agonist should be taken for immediate relief.

2.2 Exercise-Induced Bronchospasm

Use of SEREVENT DISKUS as a single agent for the prevention of EIB may be clinically indicated in patients who do not have persistent asthma. In patients with persistent asthma, use of SEREVENT DISKUS for the prevention of EIB may be clinically indicated, but the treatment of asthma should include a long-term asthma control medication, such as an inhaled corticosteroid. One inhalation of SEREVENT DISKUS at least 30 minutes before exercise has been shown to protect patients against EIB. When used intermittently as needed for prevention of EIB, this protection may last up to 9 hours in adolescents and adults and up to 12 hours in patients aged 4 to 11 years. Additional doses of SEREVENT should not be used for 12 hours after the administration of this drug. Patients who are receiving SEREVENT DISKUS twice daily should not use additional SEREVENT for prevention of EIB.

2.3 Chronic Obstructive Pulmonary Disease

For maintenance treatment of bronchospasm associated with COPD (including chronic bronchitis and emphysema), the dosage for adults is 1 inhalation (50 mcg) twice daily (morning and evening, approximately 12 hours apart).

3 DOSAGE FORMS AND STRENGTHS

Disposable teal green device with 60 blisters containing salmeterol (50 mcg) as an oral inhalation powder formulation. An institutional pack containing 28 blisters is also available.

4 CONTRAINDICATIONS

Because of the risk of asthma-related death and hospitalization, use of SEREVENT DISKUS for the treatment of asthma without concomitant use of a long-term asthma control medication, such as an inhaled corticosteroid, is contraindicated [see Warnings and Precautions (5.1)].

SEREVENT DISKUS is contraindicated as primary treatment of status asthmaticus or other acute episodes of asthma or COPD where intensive measures are required [see Warnings and Precautions (5.2)].

SEREVENT DISKUS is contraindicated in patients with severe hypersensitivity to milk proteins [see Warnings and Precautions (5.7), Adverse Reactions (6.3), Description (11)].

5 WARNINGS AND PRECAUTIONS

5.1 Asthma-Related Death

LABA, such as salmeterol, the active ingredient in SEREVENT DISKUS, increase the risk of asthma-related death. Currently available data are inadequate to determine whether concurrent use of inhaled corticosteroids or other long-term asthma control drugs mitigates the increased risk of asthma-related death from LABA.

Because of this risk, use of SEREVENT DISKUS for the treatment of asthma without concomitant use of a long-term asthma control medication, such as an inhaled corticosteroid, is contraindicated. Use SEREVENT DISKUS only as additional therapy for patients with asthma who are currently taking but are inadequately controlled on a long-term asthma control medication, such as an inhaled corticosteroid. Once asthma control is achieved and maintained, assess the patient at regular intervals and step down therapy (e.g., discontinue SEREVENT DISKUS) if possible without loss of asthma control and maintain the patient on a long-term asthma control medication, such as an inhaled corticosteroid. Do not use SEREVENT DISKUS for patients whose asthma is adequately controlled on low- or medium-dose inhaled corticosteroids.

Pediatric and Adolescent Patients: Available data from controlled clinical trials suggest that LABA increase the risk of asthma-related hospitalization in pediatric and adolescent patients. For pediatric and adolescent patients with asthma who require addition of a LABA to an inhaled corticosteroid, a fixed-dose combination product containing both an inhaled corticosteroid and a LABA should ordinarily be used to ensure adherence with both drugs. In cases where use of a separate long-term asthma control medication (e.g., inhaled corticosteroid) and a LABA is clinically indicated, appropriate steps must be taken to ensure adherence with both treatment components. If adherence cannot be assured, a fixed-dose combination product containing both an inhaled corticosteroid and a LABA is recommended.

The Salmeterol Multi-center Asthma Research Trial (SMART) was a large 28-week placebo-controlled US study comparing the safety of salmeterol (SEREVENT Inhalation Aerosol) with placebo, each added to usual asthma therapy, that showed an increase in asthma-related deaths in patients receiving salmeterol [see Clinical Studies (14.1)]. Given the similar basic mechanisms of action of beta2-agonists, the findings seen in the SMART study are considered a class effect.

A 16-week clinical study performed in the United Kingdom, the Salmeterol Nationwide Surveillance (SNS) study, showed results similar to the SMART study. In the SNS study, the rate of asthma-related death was numerically, though not statistically significantly, greater in patients with asthma treated with salmeterol (42 mcg twice daily) than those treated with albuterol (180 mcg 4 times daily) added to usual asthma therapy.

The SNS and SMART studies enrolled patients with asthma. No studies have been conducted that were adequate to determine whether the rate of death in patients with COPD is increased by LABA.

5.2 Deterioration of Disease and Acute Episodes

SEREVENT DISKUS should not be initiated in patients during rapidly deteriorating or potentially life-threatening episodes of asthma or COPD. SEREVENT DISKUS has not been studied in patients with acutely deteriorating asthma or COPD. The initiation of SEREVENT DISKUS in this setting is not appropriate.

Serious acute respiratory events, including fatalities, have been reported when salmeterol has been initiated in patients with significantly worsening or acutely deteriorating asthma. In most cases, these have occurred in patients with severe asthma (e.g., patients with a history of corticosteroid dependence, low pulmonary function, intubation, mechanical ventilation, frequent hospitalizations, previous life-threatening acute asthma exacerbations) and in some patients with acutely deteriorating asthma (e.g., patients with significantly increasing symptoms; increasing need for inhaled, short-acting beta2-agonists; decreasing response to usual medications; increasing need for systemic corticosteroids; recent emergency room visits; deteriorating lung function). However, these events have occurred in a few patients with less severe asthma as well. It was not possible from these reports to determine whether salmeterol contributed to these events.

Increasing use of inhaled, short-acting beta2-agonists is a marker of deteriorating asthma. In this situation, the patient requires immediate reevaluation with reassessment of the treatment regimen, giving special consideration to the possible need for adding additional inhaled corticosteroid or initiating systemic corticosteroids. Patients should not use more than 1 inhalation twice daily (morning and evening) of SEREVENT DISKUS.

SEREVENT DISKUS should not be used for the relief of acute symptoms, i.e., as rescue therapy for the treatment of acute episodes of bronchospasm. An inhaled, short-acting beta2-agonist, not SEREVENT DISKUS, should be used to relieve acute symptoms such as shortness of breath. When prescribing SEREVENT DISKUS, the physician must also provide the patient with an inhaled, short-acting beta2-agonist (e.g., albuterol) for treatment of acute symptoms.

When beginning treatment with SEREVENT DISKUS, patients who have been taking oral or inhaled, short-acting beta2-agonists on a regular basis (e.g., 4 times a day) should be instructed to discontinue the regular use of these drugs.

5.3 SEREVENT DISKUS is Not a Substitute for Corticosteroids

There are no data demonstrating that SEREVENT DISKUS has a clinical anti-inflammatory effect such as that associated with corticosteroids. When initiating and throughout treatment with SEREVENT DISKUS in patients receiving oral or inhaled corticosteroids for treatment of asthma, patients must continue taking a suitable dosage of corticosteroids to maintain clinical stability even if they feel better as a result of initiating SEREVENT DISKUS. Any change in corticosteroid dosage should be made ONLY after clinical evaluation.

5.4 Excessive Use of SEREVENT DISKUS and Use With Other Long-Acting Beta2-Agonists

As with other inhaled beta2-adrenergic drugs, SEREVENT DISKUS should not be used more often or at higher doses than recommended, or in conjunction with other medications containing LABA, as an overdose may result. Clinically significant cardiovascular effects and fatalities have been reported in association with excessive use of inhaled sympathomimetic drugs. Patients using SEREVENT DISKUS should not use an additional LABA (e.g., formoterol fumarate, arformoterol tartrate) for any reason.

5.5 Paradoxical Bronchospasm and Upper Airway Symptoms

As with other inhaled medications, SEREVENT DISKUS can produce paradoxical bronchospasm, which may be life threatening. If paradoxical bronchospasm occurs following dosing with SEREVENT DISKUS, it should be treated immediately with an inhaled, short-acting bronchodilator; SEREVENT DISKUS should be discontinued immediately; and alternative therapy should be instituted. Upper airway symptoms of laryngeal spasm, irritation, or swelling, such as stridor and choking, have been reported in patients receiving SEREVENT DISKUS.

5.6 Cardiovascular and Central Nervous System Effects

Excessive beta-adrenergic stimulation has been associated with seizures, angina, hypertension or hypotension, tachycardia with rates up to 200 beats/min, arrhythmias, nervousness, headache, tremor, palpitation, nausea, dizziness, fatigue, malaise, and insomnia [see Overdosage (10)]. Therefore, SEREVENT DISKUS, like all products containing sympathomimetic amines, should be used with caution in patients with cardiovascular disorders, especially coronary insufficiency, cardiac arrhythmias, and hypertension.

Salmeterol can produce a clinically significant cardiovascular effect in some patients as measured by pulse rate, blood pressure, and/or symptoms. Although such effects are uncommon after administration of salmeterol at recommended doses, if they occur, the drug may need to be discontinued. In addition, beta-agonists have been reported to produce ECG changes, such as flattening of the T wave, prolongation of the QTc interval, and ST segment depression. The clinical significance of these findings is unknown. Large doses of inhaled or oral salmeterol (12 to 20 times the recommended dose) have been associated with clinically significant prolongation of the QTc interval, which has the potential for producing ventricular arrhythmias. Fatalities have been reported in association with excessive use of inhaled sympathomimetic drugs.

5.7 Immediate Hypersensitivity Reactions

Immediate hypersensitivity reactions may occur after administration of SEREVENT DISKUS, as demonstrated by cases of urticaria, angioedema, rash, and bronchospasm. There have been reports of anaphylactic reactions in patients with severe milk protein allergy; therefore, patients with severe milk protein allergy should not take SEREVENT DISKUS [see Contraindications (4)].

5.8 Drug Interactions With Strong Cytochrome P450 3A4 Inhibitors

Because of the potential for drug interactions and the potential for increased risk of cardiovascular adverse events, the concomitant use of SEREVENT DISKUS with strong cytochrome P450 3A4 (CYP3A4) inhibitors (e.g., ketoconazole, ritonavir, atazanavir, clarithromycin, indinavir, itraconazole, nefazodone, nelfinavir, saquinavir, telithromycin) is not recommended [see Drug Interactions (7.1)].

5.9 Coexisting Conditions

SEREVENT DISKUS, like all medications containing sympathomimetic amines, should be used with caution in patients with convulsive disorders or thyrotoxicosis and in those who are unusually responsive to sympathomimetic amines. Doses of the related beta2-adrenoceptor agonist albuterol, when administered intravenously, have been reported to aggravate preexisting diabetes mellitus and ketoacidosis.

5.10 Hypokalemia and Hyperglycemia

Beta-adrenergic agonist medications may produce significant hypokalemia in some patients, possibly through intracellular shunting, which has the potential to produce adverse cardiovascular effects [see Clinical Pharmacology (12.2)]. The decrease in serum potassium is usually transient, not requiring supplementation. Clinically significant and dose-related changes in blood glucose and/or serum potassium were seen infrequently during clinical studies with SEREVENT DISKUS at recommended doses.

6 ADVERSE REACTIONS

LABA, including salmeterol, the active ingredient in SEREVENT DISKUS, increase the risk of asthma-related death. Data from a large 28-week placebo-controlled US study that compared the safety of salmeterol (SEREVENT Inhalation Aerosol) or placebo added to usual asthma therapy showed an increase in asthma-related deaths in patients receiving salmeterol. Available data from controlled clinical trials suggest that LABA increase the risk of asthma-related hospitalization in pediatric and adolescent patients [see Warnings and Precautions (5.1), Clinical Studies (14.1)].

Because clinical trials are conducted under widely varying conditions, adverse reaction rates observed in the clinical trials of a drug cannot be directly compared with rates in the clinical trials of another drug and may not reflect the rates observed in practice.

6.1 Clinical Trials Experience in Asthma

Adult and Adolescent Patients Aged 12 Years and Older: Two multicenter, 12-week, controlled studies evaluated twice-daily doses of SEREVENT DISKUS in patients aged 12 years and older with asthma. Table 1 reports the incidence of adverse reactions in these 2 studies.

Table 1. Adverse Reaction Incidence in Two 12-Week Clinical Trials in Adult and Adolescent Patients With Asthma
Adverse Event | Percent of Patients
Adverse Event | Placebo; (N = 152) | SEREVENT DISKUS; 50 mcg; Twice Daily; (N = 149) | Albuterol Inhalation Aerosol; 180 mcg; 4 Times Daily; (N = 150)
Ear, nose, and throat
Nasal/sinus congestion, pallor | 6 | 9 | 8
Rhinitis | 4 | 5 | 4
Neurological
Headache | 9 | 13 | 12
Respiratory
Asthma | 1 | 3 | <1
Tracheitis/bronchitis | 4 | 7 | 3
Influenza | 2 | 5 | 5

Table 1 includes all events (whether considered drug-related or nondrug-related by the investigator) that occurred at a rate of 3% or greater in the group receiving SEREVENT DISKUS and were more common than in the placebo group.

Pharyngitis, sinusitis, upper respiratory tract infection, and cough occurred at ≥3% but were more common in the placebo group. However, throat irritation has been described at rates exceeding that of placebo in other controlled clinical trials.

Additional Adverse Reactions: Other adverse reactions not previously listed, whether considered drug-related or not by the investigators, that were reported more frequently by patients with asthma treated with SEREVENT DISKUS compared with patients treated with placebo include the following: contact dermatitis, eczema, localized aches and pains, nausea, oral mucosal abnormality, pain in joint, paresthesia, pyrexia of unknown origin, sinus headache, and sleep disturbance.

Pediatric Patients Aged 4 to 11 Years: Two multicenter, 12-week, controlled studies have evaluated twice-daily doses of SEREVENT DISKUS in patients aged 4 to 11 years with asthma. Table 2 includes all events (whether considered drug-related or nondrug-related by the investigator) that occurred at a rate of 3% or greater in the group receiving SEREVENT DISKUS and were more common than in the placebo group.

Table 2. Adverse Reaction Incidence in Two 12-Week Pediatric Clinical Trials in Patients With Asthma
Adverse Event | Percent of Patients
Adverse Event | Placebo; (N = 215) | SEREVENT DISKUS; 50 mcg; Twice Daily; (N = 211) | Albuterol; Inhalation Aerosol; 200 mcg; 4 Times Daily; (N = 115)
Ear, nose, and throat
Ear signs and symptoms | 3 | 4 | 9
Pharyngitis | 3 | 6 | 3
Neurological
Headache | 14 | 17 | 20
Respiratory
Asthma | 2 | 4 | <1
Skin
Skin rashes | 3 | 4 | 2
Urticaria | 0 | 3 | 2

The following events were reported at an incidence of >1% in the salmeterol group and with a higher incidence than in the albuterol and placebo groups: gastrointestinal signs and symptoms, lower respiratory signs and symptoms, photodermatitis, and arthralgia and articular rheumatism.

In clinical trials evaluating concurrent therapy of salmeterol with inhaled corticosteroids, adverse events were consistent with those previously reported for salmeterol, or with events that would be expected with the use of inhaled corticosteroids.

Laboratory Test Abnormalities: Elevation of hepatic enzymes was reported in ≥1% of patients in clinical trials. The elevations were transient and did not lead to discontinuation from the studies. In addition, there were no clinically relevant changes noted in glucose or potassium.

6.2 Clinical Trials Experience in Chronic Obstructive Pulmonary Disease

Two multicenter, 24-week, controlled studies have evaluated twice-daily doses of SEREVENT DISKUS in patients with COPD. For presentation (Table 3), the placebo data from a third trial, identical in design, patient entrance criteria, and overall conduct but comparing fluticasone propionate with placebo, were integrated with the placebo data from these 2 studies (total N = 341 for salmeterol and 576 for placebo).

Table 3. Adverse Reactions With ≥3% Incidence in US Controlled Clinical Trials With SEREVENT DISKUS in Patients With Chronic Obstructive Pulmonary Diseasea
Adverse Event | Percent of Patients
Adverse Event | Placebo; (N = 576) | SEREVENT DISKUS; 50 mcg Twice Daily; (N = 341)
Cardiovascular
Hypertension | 2 | 4
Ear, nose, and throat
Throat irritation | 6 | 7
Nasal congestion/blockage | 3 | 4
Sinusitis | 2 | 4
Ear signs and symptoms | 1 | 3
Gastrointestinal
Nausea and vomiting | 3 | 3
Lower respiratory
Cough | 4 | 5
Rhinitis | 2 | 4
Viral respiratory infection | 4 | 5
Musculoskeletal
Musculoskeletal pain | 10 | 12
Muscle cramps and spasms | 1 | 3
Neurological
Headache | 11 | 14
Dizziness | 2 | 4
Average duration of exposure (days) | 128.9 | 138.5

aTable 3 includes all events (whether considered drug-related or nondrug-related by the investigator) that occurred at a rate of 3% or greater in the group receiving SEREVENT DISKUS and were more common in the group receiving SEREVENT DISKUS than in the placebo group.

Additional Adverse Reactions: Other events occurring in the group receiving SEREVENT DISKUS that occurred at a frequency of ≥1% and were more common than in the placebo group were as follows: anxiety; arthralgia and articular rheumatism; bone and skeletal pain; candidiasis mouth/throat; dental discomfort and pain; dyspeptic symptoms; edema and swelling; gastrointestinal infections; hyperglycemia; hyposalivation; keratitis and conjunctivitis; lower respiratory signs and symptoms; migraines; muscle pain; muscle stiffness, tightness, and rigidity; musculoskeletal inflammation; pain; and skin rashes.

Adverse reactions to salmeterol are similar in nature to those seen with other selective beta2-adrenoceptor agonists, e.g., tachycardia; palpitations; immediate hypersensitivity reactions, including urticaria, angioedema, rash, bronchospasm; headache; tremor; nervousness; and paradoxical bronchospasm.

Laboratory Abnormalities: There were no clinically relevant changes in these trials. Specifically, no changes in potassium were noted.

6.3 Postmarketing Experience

In addition to adverse reactions reported from clinical trials, the following adverse reactions have been identified during postapproval use of salmeterol. Because these reactions are reported voluntarily from a population of uncertain size, it is not always possible to reliably estimate their frequency or establish a causal relationship to drug exposure. These events have been chosen for inclusion due to either their seriousness, frequency of reporting, or causal connection to salmeterol or a combination of these factors.

In extensive US and worldwide postmarketing experience with salmeterol, serious exacerbations of asthma, including some that have been fatal, have been reported. In most cases, these have occurred in patients with severe asthma and/or in some patients in whom asthma has been acutely deteriorating [see Warnings and Precautions (5.2)], but they have also occurred in a few patients with less severe asthma. It was not possible from these reports to determine whether salmeterol contributed to these events.

Cardiovascular: Arrhythmias (including atrial fibrillation, supraventricular tachycardia, extrasystoles) and anaphylaxis.

Non-Site Specific: Very rare anaphylactic reaction in patients with severe milk protein allergy.

Respiratory: Reports of upper airway symptoms of laryngeal spasm, irritation, or swelling such as stridor or choking; oropharyngeal irritation.

7 DRUG INTERACTIONS

7.1 Inhibitors of Cytochrome P450 3A4

In a drug interaction study in 20 healthy subjects, coadministration of salmeterol (50 mcg twice daily) and ketoconazole (400 mg once daily) for 7 days resulted in greater systemic exposure to salmeterol (AUC increased 16-fold and Cmax increased 1.4-fold). Three (3) subjects were withdrawn due to beta2-agonist side effects (2 with prolonged QTc and 1 with palpitations and sinus tachycardia). Although there was no statistical effect on the mean QTc, coadministration of salmeterol and ketoconazole was associated with more frequent increases in QTc duration compared with salmeterol and placebo administration. Due to the potential increased risk of cardiovascular adverse events, the concomitant use of salmeterol with strong CYP3A4 inhibitors (e.g., ketoconazole, ritonavir, atazanavir, clarithromycin, indinavir, itraconazole, nefazodone, nelfinavir, saquinavir, telithromycin) is not recommended.

7.2 Monoamine Oxidase Inhibitors and Tricyclic Antidepressants

SEREVENT DISKUS should be administered with extreme caution to patients being treated with monoamine oxidase inhibitors or tricyclic antidepressants, or within 2 weeks of discontinuation of such agents, because the action of salmeterol on the vascular system may be potentiated by these agents.

7.3 Beta-Adrenergic Receptor Blocking Agents

Beta-blockers not only block the pulmonary effect of beta-agonists, such as SEREVENT DISKUS, but may also produce severe bronchospasm in patients with asthma or COPD. Therefore, patients with asthma or COPD should not normally be treated with beta-blockers. However, under certain circumstances, there may be no acceptable alternatives to the use of beta-adrenergic blocking agents for these patients; cardioselective beta-blockers could be considered, although they should be administered with caution.

7.4 Diuretics

The ECG changes and/or hypokalemia that may result from the administration of nonpotassium-sparing diuretics (such as loop or thiazide diuretics) can be acutely worsened by beta-agonists, especially when the recommended dose of the beta-agonist is exceeded. Although the clinical relevance of these effects is not known, caution is advised in the coadministration of SEREVENT DISKUS with nonpotassium-sparing diuretics.

8 USE IN SPECIFIC POPULATIONS

8.1 Pregnancy

Teratogenic Effects: Pregnancy Category C. There are no adequate and well-controlled studies with SEREVENT DISKUS in pregnant women. SEREVENT DISKUS should be used during pregnancy only if the potential benefit justifies the potential risk to the fetus.

No teratogenic effects occurred in rats at oral doses approximately 160 times the maximum recommended daily inhalation dose (MRHD) on an mg/m^2 basis. In pregnant Dutch rabbits administered oral doses approximately 50 times the MRHD based on comparison of the AUCs, salmeterol exhibited fetal toxic effects characteristically resulting from beta-adrenoceptor stimulation. These included precocious eyelid openings, cleft palate, sternebral fusion, limb and paw flexures, and delayed ossification of the frontal cranial bones. No such effects occurred at an oral dose approximately 20 times the MRHD based on comparison of the AUCs.

New Zealand White rabbits were less sensitive since only delayed ossification of the frontal cranial bones was seen at an oral dose approximately 1,600 times the MRHD on an mg/m^2 basis. Extensive use of other beta-agonists has provided no evidence that these class effects in animals are relevant to their use in humans.

8.2 Labor and Delivery

There are no well-controlled human studies that have investigated effects of salmeterol on preterm labor or labor at term. Because of the potential for beta-agonist interference with uterine contractility, use of SEREVENT DISKUS during labor should be restricted to those patients in whom the benefits clearly outweigh the risks.

8.3 Nursing Mothers

Plasma levels of salmeterol, a component of SEREVENT DISKUS, after inhaled therapeutic doses are very low. In rats, salmeterol xinafoate is excreted in the milk. Since there are no data from controlled trials on the use of salmeterol by nursing mothers, a decision should be made whether to discontinue nursing or to discontinue SEREVENT DISKUS, taking into account the importance of SEREVENT DISKUS to the mother. Caution should be exercised when SEREVENT DISKUS is administered to a nursing woman.

8.4 Pediatric Use

Available data from controlled clinical trials suggest that LABA increase the risk of asthma-related hospitalization in pediatric and adolescent patients. For pediatric and adolescent patients with asthma who require addition of a LABA to an inhaled corticosteroid, a fixed-dose combination product containing both an inhaled corticosteroid and a LABA should ordinarily be used to ensure adherence with both drugs [see Indications and Usage (1.1), Warnings and Precautions (5.1)].

The safety and efficacy of SEREVENT DISKUS in adolescents (aged 12 years and older) has been established based on adequate and well-controlled trials conducted in adults and adolescents [see Clinical Studies (14.1)]. A large 28-week placebo-controlled US study comparing salmeterol (SEREVENT Inhalation Aerosol) and placebo, each added to usual asthma therapy, showed an increase in asthma-related deaths in patients receiving salmeterol [see Clinical Studies (14.1)]. Post-hoc analyses in pediatric patients aged 12 to 18 years were also performed. Pediatric patients accounted for approximately 12% of patients in each treatment arm. Respiratory-related death or life-threatening experience occurred at a similar rate in the salmeterol group (0.12% [2/1,653]) and the placebo group (0.12% [2/1,622]; relative risk: 1.0 [95% CI: 0.1, 7.2]). All-cause hospitalization, however, was increased in the salmeterol group (2% [35/1,653]) versus the placebo group (<1% [16/1,622]; relative risk: 2.1 [95% CI: 1.1, 3.7]).

The safety and efficacy of SEREVENT DISKUS have been evaluated in over 2,500 patients aged 4 to 11 years with asthma, 346 of whom were administered SEREVENT DISKUS for 1 year. Based on available data, no adjustment of dosage of SEREVENT DISKUS in pediatric patients is warranted for either asthma or EIB.

In 2 randomized, double-blind, controlled clinical trials of 12 weeks’ duration, SEREVENT DISKUS 50 mcg was administered to 211 pediatric patients with asthma who did and who did not receive concurrent inhaled corticosteroids. The efficacy of SEREVENT DISKUS was demonstrated over the 12-week treatment period with respect to peak expiratory flow (PEF) and forced expiratory volume in 1 second (FEV1). SEREVENT DISKUS was effective in demographic subgroups (gender and age) of the population.

In 2 randomized studies in children aged 4 to 11 years with asthma and EIB, a single 50-mcg dose of SEREVENT DISKUS prevented EIB when dosed 30 minutes prior to exercise, with protection lasting up to 11.5 hours in repeat testing following this single dose in many patients.

8.5 Geriatric Use

Of the total number of adolescent and adult patients with asthma who received SEREVENT DISKUS in chronic dosing clinical trials, 209 were aged 65 years or older. Of the total number of patients with COPD who received SEREVENT DISKUS in chronic dosing clinical trials, 167 were aged 65 years or older and 45 were aged 75 years or older. No apparent differences in the safety of SEREVENT DISKUS were observed when geriatric patients were compared with younger patients in clinical trials. As with other beta2-agonists, however, special caution should be observed when using SEREVENT DISKUS in geriatric patients who have concomitant cardiovascular disease that could be adversely affected by this class of drug. Data from the trials in patients with COPD suggested a greater effect on FEV1 of SEREVENT DISKUS in the <65 years age-group, as compared with the ≥65 years age-group. However, based on available data, no adjustment of dosage of SEREVENT DISKUS in geriatric patients is warranted.

8.6 Hepatic Impairment

The pharmacokinetics of salmeterol base has not been studied in patients with hepatic impairment. Since salmeterol is predominantly cleared by hepatic metabolism, liver function impairment may lead to accumulation of salmeterol in plasma. Therefore, patients with hepatic disease should be closely monitored.

10 OVERDOSAGE

The expected signs and symptoms with overdosage of SEREVENT DISKUS are those of excessive beta-adrenergic stimulation and/or occurrence or exaggeration of any of the following: seizures, angina, hypertension or hypotension, tachycardia with rates up to 200 beats/min, arrhythmias, nervousness, headache, tremor, muscle cramps, dry mouth, palpitation, nausea, dizziness, fatigue, malaise, insomnia. Overdosage with SEREVENT DISKUS can lead to clinically significant prolongation of the QTc interval, which can produce ventricular arrhythmias. Other signs of overdosage may include hypokalemia and hyperglycemia.

As with all sympathomimetic medications, cardiac arrest and even death may be associated with abuse of SEREVENT DISKUS.

Treatment consists of discontinuation of SEREVENT DISKUS together with appropriate symptomatic therapy. The judicious use of a cardioselective beta-receptor blocker may be considered, bearing in mind that such medication can produce bronchospasm. There is insufficient evidence to determine if dialysis is beneficial for overdosage of SEREVENT DISKUS. Cardiac monitoring is recommended in cases of overdosage.

No deaths were seen in rats given salmeterol at an inhalation dose of 2.9 mg/kg (approximately 240 and 110 times the MRHD for adults and children, respectively, on an mg/m^2 basis) and in dogs at an inhalation dose of 0.7 mg/kg (approximately 190 and 90 times the MRHD for adults and children, respectively, on an mg/m^2 basis). By the oral route, no deaths occurred in mice at 150 mg/kg (approximately 6,100 and 2,900 times the MRHD for adults and children, respectively, on an mg/m^2 basis) and in rats at 1,000 mg/kg (approximately 81,000 and 38,000 times the MRHD for adults and children, respectively, on an mg/m^2 basis).

11 DESCRIPTION

SEREVENT DISKUS contains salmeterol xinafoate as the racemic form of the 1-hydroxy-2-naphthoic acid salt of salmeterol. The active component of the formulation is salmeterol base, a selective beta2-adrenergic bronchodilator. The chemical name of salmeterol xinafoate is 4-hydroxy-α^1-[[[6-(4-phenylbutoxy)hexyl]amino]methyl]-1,3-benzenedimethanol, 1-hydroxy-2-naphthalenecarboxylate. Salmeterol xinafoate has the following chemical structure:

Salmeterol xinafoate is a white powder with a molecular weight of 603.8, and the empirical formula is C25H37NO4•C11H8O3. It is freely soluble in methanol; slightly soluble in ethanol, chloroform, and isopropanol; and sparingly soluble in water.

SEREVENT DISKUS is a specially designed plastic device containing a double-foil blister strip of a powder formulation of salmeterol xinafoate intended for oral inhalation only. Each blister on the double-foil strip within the device contains 50 mcg of salmeterol administered as the salmeterol xinafoate salt in 12.5 mg of formulation containing lactose (which contains milk proteins). After a blister containing medication is opened by activating the device, the medication is dispersed into the airstream created by the patient inhaling through the mouthpiece.

Under standardized in vitro test conditions, SEREVENT DISKUS delivers 47 mcg when tested at a flow rate of 60 L/min for 2 seconds. In adult patients with obstructive lung disease and severely compromised lung function (mean FEV1 20% to 30% of predicted), mean peak inspiratory flow (PIF) through a DISKUS® inhalation device was 82.4 L/min (range: 46.1 to 115.3 L/min).

The actual amount of drug delivered to the lung will depend on patient factors, such as inspiratory flow profile.

12 CLINICAL PHARMACOLOGY

12.1 Mechanism of Action

Salmeterol is a selective LABA. In vitro studies show salmeterol to be at least 50 times more selective for beta2-adrenoceptors than albuterol. Although beta2-adrenoceptors are the predominant adrenergic receptors in bronchial smooth muscle and beta1-adrenoceptors are the predominant receptors in the heart, there are also beta2-adrenoceptors in the human heart comprising 10% to 50% of the total beta-adrenoceptors. The precise function of these receptors has not been established, but their presence raises the possibility that even highly selective beta2-agonists may have cardiac effects.

The pharmacologic effects of beta2-adrenoceptor agonist drugs, including salmeterol, are at least in part attributable to stimulation of intracellular adenyl cyclase, the enzyme that catalyzes the conversion of adenosine triphosphate (ATP) to cyclic-3′,5′-adenosine monophosphate (cyclic AMP). Increased cyclic AMP levels cause relaxation of bronchial smooth muscle and inhibition of release of mediators of immediate hypersensitivity from cells, especially from mast cells.

In vitro tests show that salmeterol is a potent and long-lasting inhibitor of the release of mast cell mediators, such as histamine, leukotrienes, and prostaglandin D2, from human lung. Salmeterol inhibits histamine-induced plasma protein extravasation and inhibits platelet-activating factor–induced eosinophil accumulation in the lungs of guinea pigs when administered by the inhaled route. In humans, single doses of salmeterol administered via inhalation aerosol attenuate allergen-induced bronchial hyper-responsiveness.

12.2 Pharmacodynamics

Inhaled salmeterol, like other beta-adrenergic agonist drugs, can in some patients produce dose-related cardiovascular effects and effects on blood glucose and/or serum potassium [see Warnings and Precautions (5.6, 5.10)]. The cardiovascular effects (heart rate, blood pressure) associated with salmeterol inhalation aerosol occur with similar frequency, and are of similar type and severity, as those noted following albuterol administration.

The effects of rising doses of salmeterol and standard inhaled doses of albuterol were studied in volunteers and in patients with asthma. Salmeterol doses up to 84 mcg administered as inhalation aerosol resulted in heart rate increases of 3 to 16 beats/min, about the same as albuterol dosed at 180 mcg by inhalation aerosol (4 to 10 beats/min). Adolescent and adult patients receiving 50-mcg doses of salmeterol inhalation powder (N = 60) underwent continuous electrocardiographic monitoring during two 12-hour periods after the first dose and after 1 month of therapy, and no clinically significant dysrhythmias were noted. Also, pediatric patients receiving 50-mcg doses of salmeterol inhalation powder (N = 67) underwent continuous electrocardiographic monitoring during two 12-hour periods after the first dose and after 3 months of therapy, and no clinically significant dysrhythmias were noted.

In 24-week clinical studies in patients with COPD, the incidence of clinically significant abnormalities on the predose electrocardiograms (ECGs) at Weeks 12 and 24 in patients who received salmeterol 50 mcg was not different compared with placebo.

No effect of treatment with salmeterol 50 mcg was observed on pulse rate and systolic and diastolic blood pressure in a subset of patients with COPD who underwent 12-hour serial vital sign measurements after the first dose (N = 91) and after 12 weeks of therapy (N = 74). Median changes from baseline in pulse rate and systolic and diastolic blood pressure were similar for patients receiving either salmeterol or placebo [see Adverse Reactions (6.1)].

Concomitant Use of SEREVENT DISKUS With Other Respiratory Medications: Short-Acting Beta2-Agonists: In two 12-week repetitive-dose adolescent and adult clinical trials in patients with asthma (N = 149), the mean daily need for additional beta2-agonist in patients using SEREVENT DISKUS was approximately 1½ inhalations/day. Twenty-six percent (26%) of the patients in these trials used between 8 and 24 inhalations of short-acting beta-agonist per day on 1 or more occasions. Nine percent (9%) of the patients in these trials averaged over 4 inhalations/day over the course of the 12-week trials. No increase in frequency of cardiovascular events was observed among the 3 patients who averaged 8 to 11 inhalations/day; however, the safety of concomitant use of more than 8 inhalations/day of short-acting beta2-agonist with SEREVENT DISKUS has not been established. In 29 patients who experienced worsening of asthma while receiving SEREVENT DISKUS during these trials, albuterol therapy administered via either nebulizer or inhalation aerosol (1 dose in most cases) led to improvement in FEV1 and no increase in occurrence of cardiovascular adverse events.

In 2 clinical trials in patients with COPD, the mean daily need for additional beta2-agonist for patients using SEREVENT DISKUS was approximately 4 inhalations/day. Twenty-four percent (24%) of the patients using SEREVENT DISKUS in these trials averaged 6 or more inhalations of albuterol per day over the course of the 24-week trials. No increase in frequency of cardiovascular adverse reactions was observed among patients who averaged 6 or more inhalations per day.

Methylxanthines: The concurrent use of intravenously or orally administered methylxanthines (e.g., aminophylline, theophylline) by patients receiving salmeterol has not been completely evaluated. In 1 clinical asthma trial, 87 patients receiving SEREVENT Inhalation Aerosol 42 mcg twice daily concurrently with a theophylline product had adverse event rates similar to those in 71 patients receiving SEREVENT Inhalation Aerosol without theophylline. Resting heart rates were slightly higher in the patients on theophylline but were little affected by therapy with SEREVENT Inhalation Aerosol.

In 2 clinical trials in patients with COPD, 39 patients receiving SEREVENT DISKUS concurrently with a theophylline product had adverse event rates similar to those in 302 patients receiving SEREVENT DISKUS without theophylline. Based on the available data, the concomitant administration of methylxanthines with SEREVENT DISKUS did not alter the observed adverse event profile.

Cromoglycate: In clinical trials, inhaled cromolyn sodium did not alter the safety profile of salmeterol when administered concurrently.

12.3 Pharmacokinetics

Salmeterol xinafoate, an ionic salt, dissociates in solution so that the salmeterol and 1-hydroxy-2-naphthoic acid (xinafoate) moieties are absorbed, distributed, metabolized, and eliminated independently. Salmeterol acts locally in the lung; therefore, plasma levels do not predict therapeutic effect.

Absorption: Because of the small therapeutic dose, systemic levels of salmeterol are low or undetectable after inhalation of recommended doses (50 mcg of salmeterol inhalation powder twice daily). Following chronic administration of an inhaled dose of 50 mcg of salmeterol inhalation powder twice daily, salmeterol was detected in plasma within 5 to 45 minutes in 7 patients with asthma; plasma concentrations were very low, with mean peak concentrations of 167 pg/mL at 20 minutes and no accumulation with repeated doses.

Distribution: The percentage of salmeterol bound to human plasma proteins averages 96% in vitro over the concentration range of 8 to 7,722 ng of salmeterol base per milliliter, much higher concentrations than those achieved following therapeutic doses of salmeterol.

Metabolism: Salmeterol base is extensively metabolized by hydroxylation, with subsequent elimination predominantly in the feces. No significant amount of unchanged salmeterol base was detected in either urine or feces.

An in vitro study using human liver microsomes showed that salmeterol is extensively metabolized to α-hydroxysalmeterol (aliphatic oxidation) by CYP3A4. Ketoconazole, a strong inhibitor of CYP3A4, essentially completely inhibited the formation of α-hydroxysalmeterol in vitro.

Elimination: In 2 healthy adult subjects who received 1 mg of radiolabeled salmeterol (as salmeterol xinafoate) orally, approximately 25% and 60% of the radiolabeled salmeterol was eliminated in urine and feces, respectively, over a period of 7 days. The terminal elimination half-life was about 5.5 hours (1 volunteer only).

The xinafoate moiety has no apparent pharmacologic activity. The xinafoate moiety is highly protein bound (>99%) and has a long elimination half-life of 11 days.

Drug Interactions: Inhibitors of Cytochrome P450 3A4: Ketoconazole: In a placebo-controlled crossover drug interaction study in 20 healthy male and female subjects, coadministration of salmeterol (50 mcg twice daily) and the strong CYP3A4 inhibitor ketoconazole (400 mg once daily) for 7 days resulted in a significant increase in plasma salmeterol exposure as determined by a 16-fold increase in AUC (ratio with and without ketoconazole 15.76 [90% CI: 10.66, 23.31]) mainly due to increased bioavailability of the swallowed portion of the dose. Peak plasma salmeterol concentrations were increased by 1.4-fold (90% CI: 1.23, 1.68). Three (3) out of 20 subjects (15%) were withdrawn from salmeterol and ketoconazole coadministration due to beta-agonist–mediated systemic effects (2 with QTc prolongation and 1 with palpitations and sinus tachycardia). Coadministration of salmeterol and ketoconazole did not result in a clinically significant effect on mean heart rate, mean blood potassium, or mean blood glucose. Although there was no statistical effect on the mean QTc, coadministration of salmeterol and ketoconazole was associated with more frequent increases in QTc duration compared with salmeterol and placebo administration.

Erythromycin: In a repeat-dose study in 13 healthy subjects, concomitant administration of erythromycin (a moderate CYP3A4 inhibitor) and salmeterol inhalation aerosol resulted in a 40% increase in salmeterol Cmax at steady state (ratio with and without erythromycin 1.4 [90% CI: 0.96, 2.03], p = 0.12), a 3.6-beat/min increase in heart rate ([95% CI: 0.19, 7.03], p<0.04), a 5.8-msec increase in QTc interval ([95% CI: -6.14, 17.77], p = 0.34), and no change in plasma potassium.

13 NONCLINICAL TOXICOLOGY

13.1 Carcinogenesis, Mutagenesis, Impairment of Fertility

In an 18-month carcinogenicity study in CD-mice, salmeterol at oral doses of 1.4 mg/kg and above (approximately 20 times the MRHD for adults and children based on comparison of the plasma AUCs) caused a dose-related increase in the incidence of smooth muscle hyperplasia, cystic glandular hyperplasia, leiomyomas of the uterus, and ovarian cysts. No tumors were seen at 0.2 mg/kg (approximately 3 times the MRHD for adults and children based on comparison of the AUCs).

In a 24-month oral and inhalation carcinogenicity study in Sprague Dawley rats, salmeterol caused a dose-related increase in the incidence of mesovarian leiomyomas and ovarian cysts at doses of 0.68 mg/kg and above (approximately 55 and 25 times the MRHD for adults and children, respectively, on an mg/m^2 basis). No tumors were seen at 0.21 mg/kg (approximately 15 and 8 times the MRHD for adults and children, respectively, on an mg/m^2 basis). These findings in rodents are similar to those reported previously for other beta-adrenergic agonist drugs. The relevance of these findings to human use is unknown.

Salmeterol produced no detectable or reproducible increases in microbial and mammalian gene mutation in vitro. No clastogenic activity occurred in vitro in human lymphocytes or in vivo in a rat micronucleus test. No effects on fertility were identified in rats treated with salmeterol at oral doses up to 2 mg/kg (approximately 160 times the MRHD for adults on an mg/m^2 basis).

13.2 Animal Toxicology and/or Pharmacology

Preclinical: Studies in laboratory animals (minipigs, rodents, and dogs) have demonstrated the occurrence of cardiac arrhythmias and sudden death (with histologic evidence of myocardial necrosis) when beta-agonists and methylxanthines are administered concurrently. The clinical relevance of these findings is unknown.

Reproductive Toxicology Studies: No teratogenic effects occurred in rats at oral doses up to 2 mg/kg (approximately 160 times the MRHD on an mg/m^2 basis).

In Dutch rabbits administered oral doses of 1 mg/kg and above (approximately 50 times and above the MRHD based on comparison of the AUCs), salmeterol exhibited fetal toxic effects characteristically resulting from beta-adrenoceptor stimulation. These included precocious eyelid openings, cleft palate, sternebral fusion, limb and paw flexures, and delayed ossification of the frontal cranial bones. No such effects occurred at an oral dose of 0.6 mg/kg (approximately 20 times the MRHD based on comparison of the AUCs). New Zealand White rabbits were less sensitive since only delayed ossification of the frontal bones was seen at an oral dose of 10 mg/kg (approximately 1,600 times the MRHD on an mg/m^2 basis).

Salmeterol crossed the placenta following oral administration to mice and rats.

14 CLINICAL STUDIES

14.1 Asthma

The initial studies supporting the approval of SEREVENT DISKUS for the treatment of asthma did not require the regular use of inhaled corticosteroids. However, for the treatment of asthma, SEREVENT DISKUS is currently indicated only as concomitant therapy with an inhaled corticosteroid [see Indications and Usage (1.1)].

Adult and Adolescent Patients Aged 12 Years and Older: In 2 randomized double-blind studies, SEREVENT DISKUS was compared with albuterol inhalation aerosol and placebo in adolescent and adult patients with mild-to-moderate asthma (protocol defined as 50% to 80% predicted FEV1, actual mean of 67.7% at baseline), including patients who did and who did not receive concurrent inhaled corticosteroids. The efficacy of SEREVENT DISKUS was demonstrated over the 12-week period with no change in effectiveness over this time period (see Figure 1). There were no gender- or age-related differences in safety or efficacy. No development of tachyphylaxis to the bronchodilator effect was noted in these studies. FEV1 measurements (mean change from baseline) from these two 12-week studies are shown in Figure 1 for both the first and last treatment days.

First Treatment Day

Last Treatment Day (Week 12)

Figure 1. Serial 12-Hour FEV1 From Two 12-Week Clinical Trials in Patients With Asthma

Table 4 shows the treatment effects seen during daily treatment with SEREVENT DISKUS for 12 weeks in adolescent and adult patients with mild-to-moderate asthma.

Table 4. Daily Efficacy Measurements in Two 12-Week Clinical Trials (Combined Data)
Parameter | Time | Placebo | SEREVENT DISKUS | Albuterol Inhalation Aerosol
No. of randomized subjects |  | 152 | 149 | 148
Mean AM peak expiratory flow (L/min) | Baseline 12 weeks | 394 | 395 | 394
Mean AM peak expiratory flow (L/min) | Baseline 12 weeks | 396 | 427a | 394
Mean % days with no asthma symptoms | Baseline 12 weeks | 14 | 13 | 12
Mean % days with no asthma symptoms | Baseline 12 weeks | 20 | 33 | 21
Mean % nights with no awakenings | Baseline 12 weeks | 70 | 63 | 68
Mean % nights with no awakenings | Baseline 12 weeks | 73 | 85a | 71
Rescue medications (mean no. of inhalations per day) | Baseline 12 weeks | 4.2 | 4.3 | 4.3
Rescue medications (mean no. of inhalations per day) | Baseline 12 weeks | 3.3 | 1.6b | 2.2
Asthma exacerbations (%) |  | 14 | 15 | 16

aStatistically superior to placebo and albuterol (p<0.001).

bStatistically superior to placebo (p<0.001).

Maintenance of efficacy for periods up to 1 year has been documented.

SEREVENT DISKUS and SEREVENT Inhalation Aerosol were compared with placebo in 2 additional randomized double-blind clinical trials in adolescent and adult patients with mild-to-moderate asthma. SEREVENT DISKUS 50 mcg and SEREVENT Inhalation Aerosol 42 mcg, both administered twice daily, produced significant improvements in pulmonary function compared with placebo over the 12-week period. While no statistically significant differences were observed between the active treatments for any of the efficacy assessments or safety evaluations performed, there were some efficacy measures on which the metered-dose inhaler appeared to provide better results. Similar findings were noted in 2 randomized, single-dose, crossover comparisons of SEREVENT DISKUS and SEREVENT Inhalation Aerosol for the prevention of EIB. Therefore, while SEREVENT DISKUS was comparable to SEREVENT Inhalation Aerosol in clinical trials in mild-to-moderate patients with asthma, it should not be assumed that they will produce clinically equivalent outcomes in all patients.

Patients on Concomitant Inhaled Corticosteroids: In 4 clinical trials in adult and adolescent patients with asthma (N = 1,922), the effect of adding SEREVENT Inhalation Aerosol to inhaled corticosteroid therapy was evaluated over a 24-week treatment period. The studies compared the addition of salmeterol therapy to an increase (at least doubling) of the inhaled corticosteroid dose.

Two randomized, double-blind, controlled, parallel-group clinical trials (N = 997) enrolled patients (aged 18 to 82 years) with persistent asthma who were previously maintained but not adequately controlled on inhaled corticosteroid therapy. During the 2-week run-in period, all patients were switched to beclomethasone dipropionate (BDP) 168 mcg twice daily. Patients still not adequately controlled were randomized to either the addition of SEREVENT Inhalation Aerosol 42 mcg twice daily or an increase of BDP to 336 mcg twice daily. As compared with the doubled dose of BDP, the addition of SEREVENT Inhalation Aerosol resulted in statistically significantly greater improvements in pulmonary function and asthma symptoms, and statistically significantly greater reduction in supplemental albuterol use. The percent of patients who experienced asthma exacerbations overall was not different between groups (i.e., 16.2% in the group receiving SEREVENT Inhalation Aerosol versus 17.9% in the higher-dose beclomethasone dipropionate group).

Two randomized, double-blind, controlled, parallel-group clinical trials (N = 925) enrolled patients (aged 12 to 78 years) with persistent asthma who were previously maintained but not adequately controlled on prior asthma therapy. During the 2- to 4-week run-in period, all patients were switched to fluticasone propionate 88 mcg twice daily. Patients still not adequately controlled were randomized to either the addition of SEREVENT Inhalation Aerosol 42 mcg twice daily or an increase of fluticasone propionate to 220 mcg twice daily. As compared with the increased (2.5 times) dose of fluticasone propionate, the addition of SEREVENT Inhalation Aerosol resulted in statistically significantly greater improvements in pulmonary function and asthma symptoms, and statistically significantly greater reductions in supplemental albuterol use. Fewer patients receiving SEREVENT Inhalation Aerosol experienced asthma exacerbations than those receiving the higher dose of fluticasone propionate (8.8% versus 13.8%).

Table 5 shows the treatment effects seen during daily treatment with SEREVENT Inhalation Aerosol for 24 weeks in adolescent and adult patients with mild-to-moderate asthma.

Onset of Action: During the initial treatment day in several multiple-dose clinical trials with SEREVENT DISKUS in patients with asthma, the median time to onset of clinically significant bronchodilatation (≥15% improvement in FEV1) ranged from 30 to 48 minutes after a 50-mcg dose.

One hour after a single dose of 50 mcg of SEREVENT DISKUS, the majority of patients had ≥15% improvement in FEV1. Maximum improvement in FEV1 generally occurred within 180 minutes, and clinically significant improvement continued for 12 hours in most patients.

Pediatric Patients: In a randomized, double-blind, controlled study (N = 449), 50 mcg of SEREVENT DISKUS was administered twice daily to pediatric patients with asthma who did and who did not receive concurrent inhaled corticosteroids. The efficacy of salmeterol inhalation powder was demonstrated over the 12-week treatment period with respect to periodic serial PEF (36% to 39% postdose increase from baseline) and FEV1 (32% to 33% postdose increase from baseline). Salmeterol was effective in demographic subgroup analyses (gender and age) and was effective when coadministered with other inhaled asthma medications such as short-acting bronchodilators and inhaled corticosteroids. A second randomized, double-blind, placebo-controlled study (N = 207) with 50 mcg of salmeterol inhalation powder via an alternate device supported the findings of the trial with the DISKUS.

Salmeterol Multi-center Asthma Research Trial: The SMART study was a randomized double-blind study that enrolled LABA-naive patients with asthma (average age of 39 years; 71% Caucasian, 18% African American, 8% Hispanic) to assess the safety of salmeterol (SEREVENT Inhalation Aerosol) 42 mcg twice daily over 28 weeks compared with placebo when added to usual asthma therapy.

A planned interim analysis was conducted when approximately half of the intended number of patients had been enrolled (N = 26,355), which led to premature termination of the study. The results of the interim analysis showed that patients receiving salmeterol were at increased risk for fatal asthma events (see Table 5 and Figure 2). In the total population, a higher rate of asthma-related death occurred in patients treated with salmeterol than those treated with placebo (0.10% versus 0.02%, relative risk: 4.37 [95% CI: 1.25, 15.34]).

Post-hoc subpopulation analyses were performed. In Caucasians, asthma-related death occurred at a higher rate in patients treated with salmeterol than in patients treated with placebo (0.07% versus 0.01%, relative risk: 5.82 [95% CI: 0.70, 48.37]). In African Americans also, asthma-related death occurred at a higher rate in patients treated with salmeterol than those treated with placebo (0.31% versus 0.04%, relative risk: 7.26 [95% CI: 0.89, 58.94]). Although the relative risks of asthma-related death were similar in Caucasians and African Americans, the estimate of excess deaths in patients treated with salmeterol was greater in African Americans because there was a higher overall rate of asthma-related death in African American patients (see Table 5).

Post-hoc analyses in pediatric patients aged 12 to 18 years were also performed. Pediatric patients accounted for approximately 12% of patients in each treatment arm. Respiratory-related death or life-threatening experience occurred at a similar rate in the salmeterol group (0.12% [2/1,653]) and the placebo group (0.12% [2/1,622]; relative risk: 1.0 [95% CI: 0.1, 7.2]). All-cause hospitalization, however, was increased in the salmeterol group (2% [35/1,653]) versus the placebo group (<1% [16/1,622]; relative risk: 2.1 [95% CI: 1.1, 3.7]).

The data from the SMART study are not adequate to determine whether concurrent use of inhaled corticosteroids or other long-term asthma control therapy mitigates the risk of asthma-related death.

Table 5: Asthma-Related Deaths in the 28-Week Salmeterol Multi-center Asthma Research Trial (SMART)
 | Salmeterol; n (%a) | Placebo; n (%a) | Relative Riskb (95% Confidence Interval) | Excess Deaths Expressed per 10,000 Patientsc (95% Confidence Interval)
Total Populationd
Salmeterol: N = 13,176 | 13 (0.10%) |  | 4.37 (1.25, 15.34) | 8 (3, 13)
Placebo: N = 13,179 |  | 3 (0.02%)
Caucasian
Salmeterol: N = 9,281 | 6 (0.07%) |  | 5.82 (0.70, 48.37) | 6 (1, 10)
Placebo: N = 9,361 |  | 1 (0.01%)
African American
Salmeterol: N = 2,366 | 7 (0.31%) |  | 7.26 (0.89, 58.94) | 27 (8, 46)
Placebo: N = 2,319 |  | 1 (0.04%)

aLife-table 28-week estimate, adjusted according to the patients’ actual lengths of exposure to study treatment to account for early withdrawal of patients from the study.

bRelative risk is the ratio of the rate of asthma-related death in the salmeterol group and the rate in the placebo group. The relative risk indicates how many more times likely an asthma-related death occurred in the salmeterol group than in the placebo group in a 28-week treatment period.

c Estimate of the number of additional asthma-related deaths in patients treated with salmeterol in SMART, assuming 10,000 patients received salmeterol for a 28-week treatment period. Estimate calculated as the difference between the salmeterol and placebo groups in the rates of asthma-related death multiplied by 10,000.

dThe Total Population includes the following ethnic origins listed on the case report form: Caucasian, African American, Hispanic, Asian, and “Other.” In addition, the Total Population includes those patients whose ethnic origin was not reported. The results for Caucasian and African American subpopulations are shown above. No asthma-related deaths occurred in the Hispanic (salmeterol n = 996, placebo n = 999), Asian (salmeterol n = 173, placebo n = 149), or “Other” (salmeterol n = 230, placebo n = 224) subpopulations. One asthma-related death occurred in the placebo group in the subpopulation whose ethnic origin was not reported (salmeterol n = 130, placebo n = 127).

Figure 2. Cumulative Incidence of Asthma-Related Deaths in the 28-Week Salmeterol Multi-center Asthma Research Trial (SMART), by Duration of Treatment

14.2 Exercise-Induced Bronchospasm

In 2 randomized, single-dose, crossover studies in adolescents and adults with EIB (N = 52), 50 mcg of SEREVENT DISKUS prevented EIB when dosed 30 minutes prior to exercise. For some patients, this protective effect against EIB was still apparent up to 8.5 hours following a single dose (see Table 6).

Table 6. Results of 2 Exercise-Induced Bronchospasm Studies in Adolescents and Adults
 |  | Placebo; (N = 52) |  | SEREVENT DISKUS; (N = 52)
 |  | n | % Total | n | % Total
0.5-Hour postdose exercise challenge | % Fall in FEV1
0.5-Hour postdose exercise challenge | <10% | 15 | 29 | 31 | 60
0.5-Hour postdose exercise challenge | ≥10%, <20% | 3 | 6 | 11 | 21
0.5-Hour postdose exercise challenge | ≥20% | 34 | 65 | 10 | 19
Mean maximal % fall in FEV1 (SE) |  | -25% (1.8) |  | -11% (1.9)
8.5-Hour postdose exercise challenge | % Fall in FEV1
8.5-Hour postdose exercise challenge | <10% | 12 | 23 | 26 | 50
8.5-Hour postdose exercise challenge | ≥10%, <20% | 7 | 13 | 12 | 23
8.5-Hour postdose exercise challenge | ≥20% | 33 | 63 | 14 | 27
Mean maximal % fall in FEV1 (SE) |  | -27% (1.5) |  | -16% (2.0)

In 2 randomized studies in children aged 4 to 11 years with asthma and EIB (N = 50), a single 50-mcg dose of SEREVENT DISKUS prevented EIB when dosed 30 minutes prior to exercise, with protection lasting up to 11.5 hours in repeat testing following this single dose in many patients.

14.3 Chronic Obstructive Pulmonary Disease

In 2 clinical trials evaluating twice-daily treatment with SEREVENT DISKUS 50 mcg (N = 336) compared with placebo (N = 366) in patients with chronic bronchitis with airflow limitation, with or without emphysema, improvements in pulmonary function endpoints were greater with salmeterol 50 mcg than with placebo. Treatment with SEREVENT DISKUS did not result in significant improvements in secondary endpoints assessing COPD symptoms in either clinical trial. Both trials were randomized, double-blind, parallel-group studies of 24 weeks’ duration and were identical in design, patient entrance criteria, and overall conduct.

Figure 3 displays the integrated 2-hour postdose FEV1 results from the 2 clinical trials. The percent change in FEV1 refers to the change from baseline, defined as the predose value on Treatment Day 1. To account for patient withdrawals during the study, Endpoint (last evaluable FEV1) data are provided. Patients receiving SEREVENT DISKUS 50 mcg had significantly greater improvements in 2-hour postdose FEV1 at Endpoint (216 mL, 20%) compared with placebo (43 mL, 5%). Improvement was apparent on the first day of treatment and maintained throughout the 24 weeks of treatment.

Figure 3. Mean Percent Change From Baseline in Postdose FEV1 Integrated Data From 2 Trials of Patients With Chronic Bronchitis and Airflow Limitation

Onset of Action and Duration of Effect: The onset of action and duration of effect of SEREVENT DISKUS were evaluated in a subset of patients (n = 87) from 1 of the 2 clinical trials discussed above. Following the first 50-mcg dose, significant improvement in pulmonary function (mean FEV1 increase of 12% or more and at least 200 mL) occurred at 2 hours. The mean time to peak bronchodilator effect was 4.75 hours. As seen in Figure 4, evidence of bronchodilatation was seen throughout the 12-hour period. Figure 4 also demonstrates that the bronchodilating effect after 12 weeks of treatment was similar to that observed after the first dose. The mean time to peak bronchodilator effect after 12 weeks of treatment was 3.27 hours.

Figure 4. Serial 12-Hour FEV1 on the First Day and at Week 12 of Treatment

16 HOW SUPPLIED/STORAGE AND HANDLING

SEREVENT DISKUS is supplied as a disposable teal green device containing 60 blisters. The DISKUS inhalation device is packaged within a plastic-coated, moisture-protective foil pouch (NDC 0173-0521-00).

SEREVENT DISKUS is also supplied in an institutional pack of 1 disposable teal green unit containing 28 blisters. The drug product is packaged within a plastic-coated, moisture-protective foil pouch (NDC 0173-0520-00).

Store at controlled room temperature (see USP), 20º to 25ºC (68º to 77ºF) in a dry place away from direct heat or sunlight. Keep out of reach of children. The DISKUS inhalation device is not reusable. The device should be discarded 6 weeks after removal from the moisture-protective foil pouch or after all blisters have been used (when the dose indicator reads “0”), whichever comes first. Do not attempt to take the DISKUS apart.

17 PATIENT COUNSELING INFORMATION

See FDA-approved Medication Guide.

17.1 Asthma-Related Death

Patients should be informed that salmeterol increases the risk of asthma-related death and may increase the risk of asthma-related hospitalization in pediatric and adolescent patients. Patients should be informed that SEREVENT DISKUS should not be the only therapy for the treatment of asthma and must only be used as additional therapy when long-term asthma control medications (e.g., inhaled corticosteroids) do not adequately control asthma symptoms. They should also be informed that currently available data are inadequate to determine whether concurrent use of inhaled corticosteroids or other long-term asthma control drugs mitigates the increased risk of asthma-related death from LABA. Patients should be informed that when SEREVENT DISKUS is added to their treatment regimen they must continue to use their long-term asthma control medication.

17.2 Not for Acute Symptoms

SEREVENT DISKUS is not meant to relieve acute asthma symptoms or exacerbations of COPD and extra doses should not be used for that purpose. Acute symptoms should be treated with an inhaled, short-acting beta2-agonist such as albuterol. The physician should provide the patient with such medication and instruct the patient in how it should be used.

Patients should be instructed to notify their physicians immediately if they experience any of the following:

- Decreasing effectiveness of inhaled, short-acting beta2-agonists
- Need for more inhalations than usual of inhaled, short-acting beta2-agonists
- Significant decrease in lung function as outlined by the physician

Patients should not stop therapy with SEREVENT DISKUS without physician/provider guidance since symptoms may recur after discontinuation.

17.3 SEREVENT DISKUS is Not a Substitute for Corticosteroids

All patients with asthma should be advised that they must also continue regular maintenance treatment with an inhaled corticosteroid if they are taking SEREVENT DISKUS.

SEREVENT DISKUS should not be used as a substitute for oral or inhaled corticosteroids. The dosage of these medications should not be changed and they should not be stopped without consulting the physician, even if the patient feels better after initiating treatment with SEREVENT DISKUS.

17.4 Do Not Use Additional Long-Acting Beta2-Agonists

When patients are prescribed SEREVENT DISKUS, other LABA should not be used.

17.5 Risks Associated With Beta-Agonist Therapy

Patients should be informed of adverse effects associated with beta2-agonists, such as palpitations, chest pain, rapid heart rate, tremor, or nervousness.

17.6 Treatment of Exercise-Induced Bronchospasm

When used for the treatment of EIB, additional doses of SEREVENT should not be used for 12 hours. Patients who are receiving SEREVENT DISKUS twice daily should not use additional SEREVENT for prevention of EIB.

SEREVENT and DISKUS are registered trademarks of GlaxoSmithKline.

GlaxoSmithKline

Research Triangle Park, NC 27709

©2011, GlaxoSmithKline. All rights reserved.

April 2011

SRD:7PI

MEDICATION GUIDE

SEREVENT® [ser′ uh-vent] DISKUS®

(salmeterol xinafoate inhalation powder)

Read the Medication Guide that comes with SEREVENT DISKUS before you start using it and each time you get a refill. There may be new information. This Medication Guide does not take the place of talking to your healthcare provider about your medical condition or treatment.

What is the most important information I should know about SEREVENT DISKUS?

SEREVENT DISKUS can cause serious side effects, including:

1. People with asthma who take long-acting beta2-adrenergic agonist (LABA) medicines such as salmeterol (SEREVENT DISKUS), have an increased risk of death from asthma problems.
  - Call your healthcare provider if breathing problems worsen over time while using SEREVENT DISKUS. You may need a different treatment.
  - Get emergency medical care if:
    - breathing problems worsen quickly, and
    - you use your rescue inhaler medicine, but it does not relieve your breathing problems.
2. Do not use SEREVENT DISKUS as your only asthma medicine. SEREVENT DISKUS must only be used with a long-term asthma-control medicine, such as an inhaled corticosteroid.
3. When your asthma is well controlled, your healthcare provider may tell you to stop taking SEREVENT DISKUS. Your healthcare provider will decide if you can stop SEREVENT DISKUS without loss of asthma control. You will continue taking your long-term asthma-control medicine, such as an inhaled corticosteroid.
4. Children and adolescents who take LABA medicines may have an increased risk of being hospitalized for asthma problems.

What is SEREVENT DISKUS?

- SEREVENT DISKUS is a LABA medicine. LABA medicines help the muscles around the airways in your lungs stay relaxed to prevent symptoms, such as wheezing and shortness of breath. These symptoms can happen when the muscles around the airways tighten. This makes it hard to breathe. In severe cases, wheezing can stop your breathing and cause death if not treated right away.
- SEREVENT DISKUS is used for asthma, exercise-induced bronchospasm (EIB), and chronic obstructive pulmonary disease (COPD) as follows:

Asthma:

SEREVENT DISKUS is used in adults and children aged 4 years and older, with a long-term asthma control medicine, such as an inhaled corticosteroid:

- to control symptoms of asthma, and
- to prevent symptoms such as wheezing.

LABA medicines, such as SEREVENT DISKUS, increase the risk of death from asthma problems. SEREVENT DISKUS is not for adults and children with asthma who are well controlled with a long-term asthma-control medicine, such as a low to medium dose of an inhaled corticosteroid medicine.

Exercise-Induced Bronchospasm:

SEREVENT DISKUS is used to prevent wheezing caused by exercise in adults and children aged 4 years and older.

- If you have EIB only, your healthcare provider may prescribe only SEREVENT DISKUS for your condition.
- If you have EIB and asthma, your healthcare provider should also prescribe an asthma control medicine, such as an inhaled corticosteroid.

Chronic Obstructive Pulmonary Disease:

SEREVENT DISKUS is used long term, 2 times each day (morning and evening) to control symptoms of COPD and prevent wheezing in adults with COPD.

Who should not use SEREVENT DISKUS?

Do not take SEREVENT DISKUS:

- to treat your asthma without an asthma medicine known as an inhaled corticosteroid
- if you are allergic to salmeterol or any of the ingredients in SEREVENT DISKUS. Ask your healthcare provider if you are not sure. See the end of this Medication Guide for a complete list of ingredients in SEREVENT DISKUS.

What should I tell my healthcare provider before using SEREVENT DISKUS?

Tell your healthcare provider about all of your health conditions, including if you:

- have heart problems
- have high blood pressure
- have seizures
- have thyroid problems
- have diabetes
- have liver problems
- are pregnant or planning to become pregnant. It is not known if SEREVENT DISKUS may harm your unborn baby.
- are breastfeeding. It is not known if SEREVENT DISKUS passes into your milk and if it can harm your baby.
- are allergic to SEREVENT DISKUS, any other medicines, or food products. See the end of this Medication Guide for a complete list of ingredients in SEREVENT DISKUS.

Tell your healthcare provider about all the medicines you take including prescription and non-prescription medicines, vitamins, and herbal supplements. SEREVENT DISKUS and certain other medicines, especially those used to treat infections, may interact with each other. This may cause serious side effects.

Know the medicines you take. Keep a list and show it to your healthcare provider and pharmacist each time you get a new medicine.

How do I use SEREVENT DISKUS?

See the step-by-step instructions for using the SEREVENT DISKUS at the end of this Medication Guide. Do not use SEREVENT DISKUS unless your healthcare provider has taught you and you understand everything. Ask your healthcare provider or pharmacist if you have any questions.

- Children should use SEREVENT DISKUS with an adult’s help, as instructed by the child’s healthcare provider.
- Use SEREVENT DISKUS exactly as prescribed. Do not use SEREVENT DISKUS more often than prescribed.
- For asthma and COPD, the usual dose is 1 inhalation 2 times each day (morning and evening). The 2 doses should be about 12 hours apart.
- For preventing exercise-induced bronchospasm, take 1 inhalation at least 30 minutes before exercise. Do not use SEREVENT DISKUS more often than every 12 hours. Do not use extra SEREVENT DISKUS before exercise if you already use it 2 times each day.
- If you miss a dose of SEREVENT DISKUS, just skip that dose. Take your next dose at your usual time. Do not take 2 doses at one time.
- Do not use a spacer device with SEREVENT DISKUS.
- Do not breathe into SEREVENT DISKUS.
- While you are using SEREVENT DISKUS 2 times each day, do not use other medicines that contain a long-acting beta2-agonist or LABA for any reason. Ask your healthcare provider or pharmacist for a list of these medicines.
- Do not stop using SEREVENT DISKUS or any of your asthma medicines unless told to do so by your healthcare provider because your symptoms might get worse. Your healthcare provider will change your medicines as needed.
- SEREVENT DISKUS does not relieve sudden symptoms. Always have a rescue inhaler medicine with you to treat sudden symptoms. If you do not have an inhaled, short-acting bronchodilator, contact your healthcare provider to have one prescribed for you.
- Call your healthcare provider or get medical care right away if:
  - your breathing problems worsen with SEREVENT DISKUS
  - you need to use your rescue inhaler medicine more often than usual
  - your rescue inhaler medicine does not work as well for you at relieving symptoms
  - you need to use 4 or more inhalations of your rescue inhaler medicine for 2 or more days in a row
  - you use 1 whole canister of your rescue inhaler medicine in 8 weeks’ time
  - your peak flow meter results decrease. Your healthcare provider will tell you the numbers that are right for you.
  - you have asthma and your symptoms do not improve after using SEREVENT DISKUS regularly for 1 week.
  - after a change in your asthma medicines you have any worsening of your asthma symptoms or an increase in the need for your rescue inhaler medicine.

What are the possible side effects with SEREVENT DISKUS?

SEREVENT DISKUS can cause serious side effects, including:

- See “What is the most important information I should know about SEREVENT DISKUS?”

- serious allergic reactions. Call your healthcare provider or get emergency medical care if you get any of the following symptoms of a serious allergic reaction:
  - rash
  - hives
  - swelling of the face, mouth, and tongue
  - breathing problems.
- sudden breathing problems immediately after inhaling your medicine
- effects on heart
  - increased blood pressure
  - a fast and irregular heartbeat
  - chest pain
- effects on nervous system
  - tremor
  - nervousness
- changes in blood (sugar, potassium)

Common side effects of SEREVENT DISKUS include:

Asthma in adults and children:

- headache
- nasal congestion
- bronchitis
- throat irritation
- runny nose
- flu

Chronic obstructive pulmonary disease:

- headache
- musculoskeletal pain
- throat irritation
- cough
- respiratory infection

Tell your healthcare provider about any side effect that bothers you or that does not go away.

These are not all the side effects with SEREVENT DISKUS. Ask your healthcare provider or pharmacist for more information.

Call your doctor for medical advice about side effects. You may report side effects to FDA at 1-800-FDA-1088.

How do I store SEREVENT DISKUS?

- Store SEREVENT DISKUS at room temperature between 68°F to 77°F (20°C to 25°C). Keep in a dry place away from heat and sunlight.
- Safely discard SEREVENT DISKUS 6 weeks after you remove it from the foil pouch, or after the dose indicator reads “0”, whichever comes first.
- Keep SEREVENT DISKUS and all medicines out of the reach of children.

General Information about SEREVENT DISKUS

Medicines are sometimes prescribed for purposes not mentioned in a Medication Guide. Do not use SEREVENT DISKUS for a condition for which it was not prescribed. Do not give your SEREVENT DISKUS to other people, even if they have the same condition that you have. It may harm them.

This Medication Guide summarizes the most important information about SEREVENT DISKUS. If you would like more information, talk with your healthcare provider or pharmacist. You can ask your healthcare provider or pharmacist for information about SEREVENT DISKUS that was written for healthcare professionals. You can also contact the company that makes SEREVENT DISKUS (toll free) at 1-888-825-5249 or at www.serevent.com.

What are the ingredients in SEREVENT DISKUS?

Active ingredient: salmeterol xinafoate

Inactive ingredient: lactose (contains milk proteins)

Instructions for Using SEREVENT DISKUS

Follow the instructions below for using your SEREVENT DISKUS. You will breathe in (inhale) the medicine from the DISKUS. If you have any questions, ask your healthcare provider or pharmacist.

Take the SEREVENT DISKUS out of the box and foil pouch. Write the “Pouch opened” and “Use by” dates on the label on top of the DISKUS. The “Use by” date is 6 weeks from date of opening the pouch.

- The DISKUS will be in the closed position when the pouch is opened.
- The dose indicator on the top of the DISKUS tells you how many doses are left. The dose indicator number will decrease each time you use the DISKUS. After you have used 55 doses from the DISKUS, the numbers 5 to 0 will appear in red to warn you that there are only a few doses left (see Figure 1).

Figure 1

Taking a dose from the DISKUS requires the following 3 simple steps: Open, Click, Inhale.

1. OPEN

Hold the DISKUS in one hand and put the thumb of your other hand on the thumbgrip. Push your thumb away from you as far as it will go until the mouthpiece appears and snaps into position (see Figure 2).

Figure 2

2. CLICK

Hold the DISKUS in a level, flat position with the mouthpiece towards you. Slide the lever away from you as far as it will go until it clicks (see Figure 3). The DISKUS is now ready to use.

Figure 3

Every time the lever is pushed back, a dose is ready to be inhaled. This is shown by a decrease in numbers on the dose counter. To avoid releasing or wasting doses once the DISKUS is ready:

- Do not close the DISKUS.
- Do not tilt the DISKUS.
- Do not play with the lever.
- Do not move the lever more than once.

3. INHALE

Before inhaling your dose from the DISKUS, breathe out (exhale) fully while holding the DISKUS level and away from your mouth (see Figure 4). Remember, never breathe out into the DISKUS mouthpiece.

Figure 4

Put the mouthpiece to your lips (see Figure 5). Breathe in quickly and deeply through the DISKUS. Do not breathe in through your nose.

Figure 5

Remove the DISKUS from your mouth. Hold your breath for about 10 seconds, or for as long as is comfortable. Breathe out slowly.

The DISKUS delivers your dose of medicine as a very fine powder. Most patients can taste or feel the powder. Do not use another dose from the DISKUS if you do not feel or taste the medicine.

4. Close the DISKUS when you are finished taking a dose so that the DISKUS will be ready for you to take your next dose. Put your thumb on the thumbgrip and slide the thumbgrip back towards you as far as it will go (see Figure 6). The DISKUS will click shut. The lever will automatically return to its original position. The DISKUS is now ready for you to take your next scheduled dose, due in about 12 hours. (Repeat steps 1 to 4.)

Figure 6

Remember:

- Never breathe into the DISKUS.
- Never take the DISKUS apart.
- Always ready and use the DISKUS in a level, flat position.
- Do not use the DISKUS with a spacer device.
- Never wash the mouthpiece or any part of the DISKUS. Keep it dry.
- Always keep the DISKUS in a dry place.
- Never take an extra dose, even if you did not taste or feel the medicine.

This Medication Guide has been approved by the U.S. Food and Drug Administration.

SEREVENT and DISKUS are registered trademarks of GlaxoSmithKline.

GlaxoSmithKline

Research Triangle Park, NC 27709

©2010, GlaxoSmithKline. All rights reserved.

December 2010

SRD:4MG

PACKAGE LABEL

Principal Display Panel

NDC 68258-8961-06

Serevent® Diskus®

(salmeterol xinafoate inhalation powder)

50 mcg

Rx only

FOR ORAL INHALATION ONLY

Each blister contains 50 mcg of salmeterol base with lactose monohydrate.

IMPORTANT: Read the accompanying Medication Guide leaflet carefully for further information.

Discard the DISKUS® 6 weeks after removal from the overwrap. Fill in the dates on the DISKUS® appropriately.

Dosage: Use only as directed by your doctor.

Store at controlled room temperature (see USP), 20o to 25oC (68o to 77oF) in a dry place away from direct heat or sunlight.

1 DISKUS® Inhalation Device Containing 1 Foil Strip of 60 Blisters